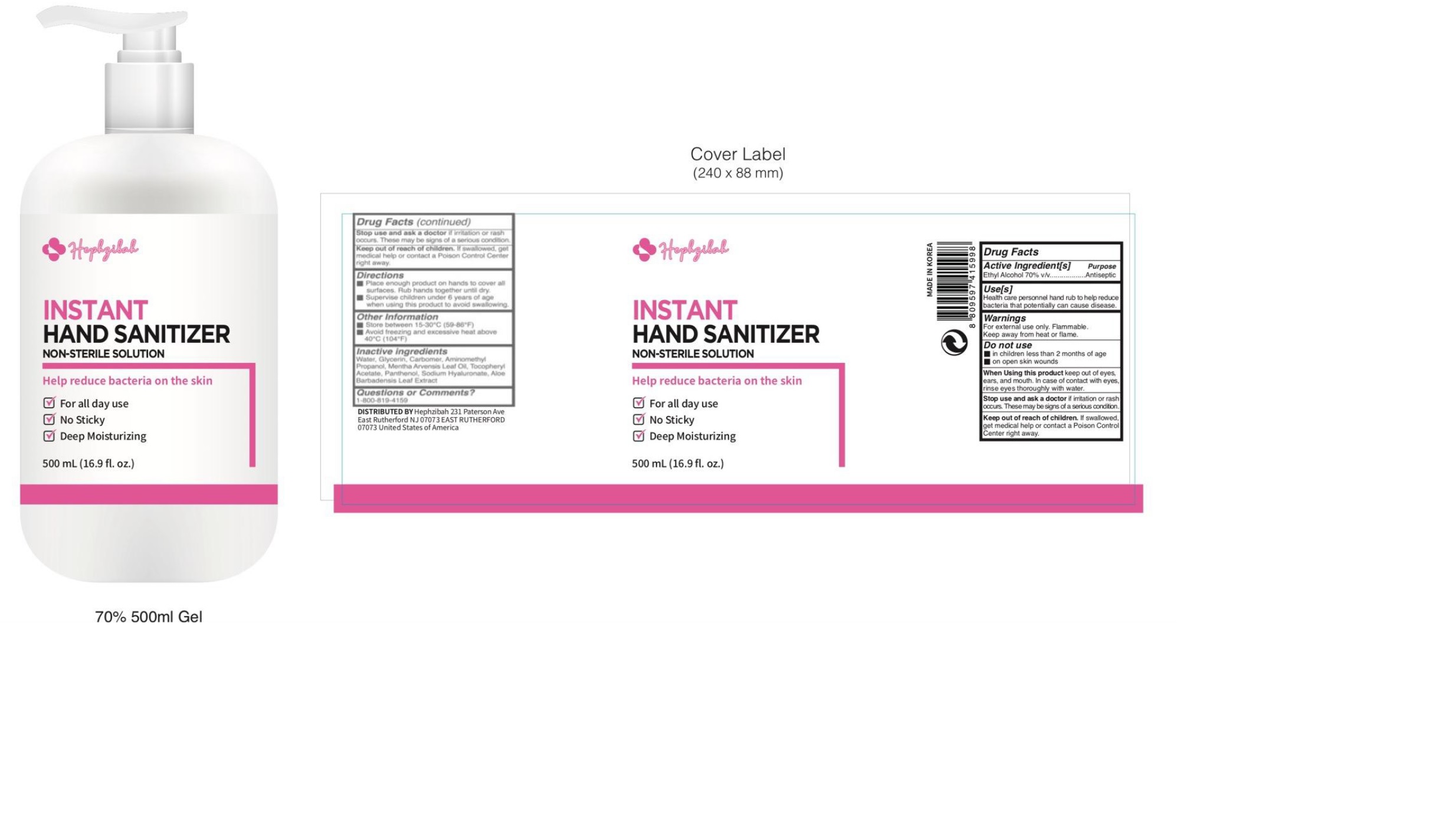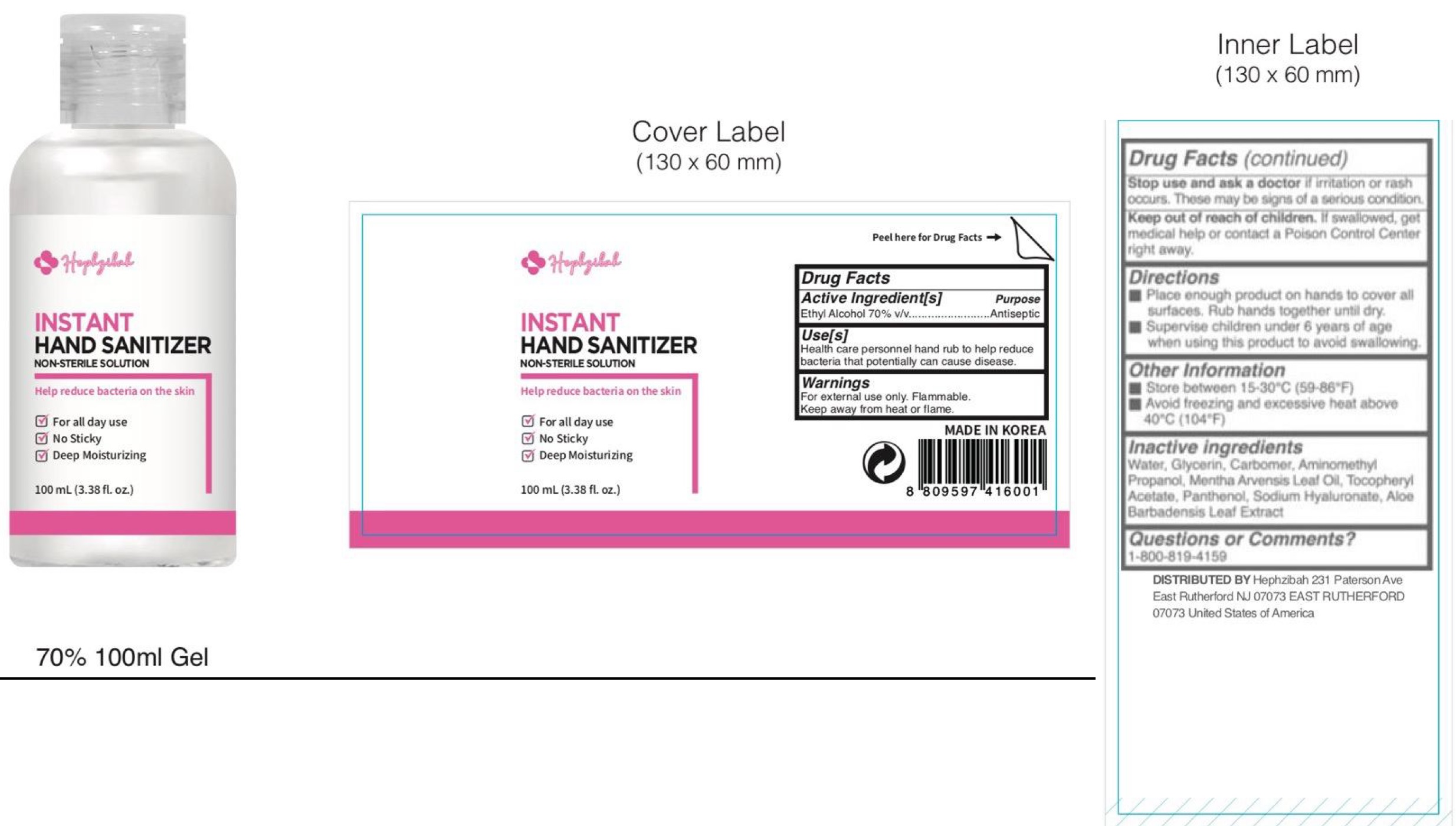 DRUG LABEL: Hephzibah Instant Hand Sanitizer
NDC: 77726-001 | Form: LIQUID
Manufacturer: Hephzibah
Category: otc | Type: HUMAN OTC DRUG LABEL
Date: 20210121

ACTIVE INGREDIENTS: ALCOHOL 0.7 mL/1 mL
INACTIVE INGREDIENTS: WATER; GLYCERIN; CARBOMER HOMOPOLYMER, UNSPECIFIED TYPE; AMINOMETHYLPROPANOL; MENTHA ARVENSIS LEAF OIL; .ALPHA.-TOCOPHEROL ACETATE; PANTHENOL; HYALURONATE SODIUM; ALOE VERA LEAF

Hephzibah Instant Hand Sanitizer

Active Ingredients(s)

Ethyl Alcohol 70% v/v

Purpose

Antiseptic

Use[s]

Health care personnel hand rub to help reduce bacteria that potentially can cause disease.

Warnings

For external use only. Flammable. Keep away from heat or flame.

Do not use

- in children less than 2 months of age
- on open skin wounds

When using this product

keep out of eyes, ears and mouth. In case of contact with eyes, rinse eyes thoroughly with water.

Stop use and ask a doctor

if irritation or rash occurs. These may be signs of a serious condition.

Keep out of reach of children.

if swallowed, get medical help or contact a Poison Control Center right away.

Directions

- Place enough product on hands to cover all surfaces. Rub hands together until dry.
- Supervise children under 6 years of age when using this product to avoid swallowing.

Other Information

- Store between 15-30°C(59-86°F)
- Avoid freezing and excessive heat above 40°C (104°F)

Inactive Ingredients

Water, Glycerin, Carbomer, Aminomethyl Propanol, Mentha Arvensis Leaf Oil, Tocopheryl Acetate, Panthenol, Sodium Hyaluronate, Aloe Barbadensis Leaf Extract

Questions or Comments?

1-800-819-4159